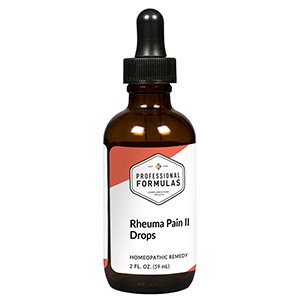 DRUG LABEL: Rheuma Pain II Drops
NDC: 63083-2058 | Form: LIQUID
Manufacturer: Professional Complementary Health Formulas
Category: homeopathic | Type: HUMAN OTC DRUG LABEL
Date: 20190815

ACTIVE INGREDIENTS: PULSATILLA MONTANA WHOLE 4 [hp_X]/59 mL; SODIUM SULFATE 6 [hp_X]/59 mL; ZANTHOXYLUM AMERICANUM BARK 6 [hp_X]/59 mL; SOLANUM DULCAMARA WHOLE 6 [hp_X]/59 mL; ARSENIC TRIOXIDE 8 [hp_X]/59 mL; RHODODENDRON AUREUM LEAF 12 [hp_X]/59 mL; ECHINACEA PURPUREA WHOLE 12 [hp_X]/59 mL; LACHESIS MUTA VENOM 12 [hp_X]/59 mL
INACTIVE INGREDIENTS: ALCOHOL; WATER

C58

ACTIVE INGREDIENTS

Pulsatilla 4X
Natrum sulphuricum 6X
Xanthoxylum fraxineum 6X
Dulcamara 6X, 12X, 30X
Arsenicum album 8X
Rhododendron chrysanthum 12X
Echinacea purpurea 12X, 30X, 100X
Lachesis mutus 12X, 30X, 100X

QUESTIONS

Professional Formulas

PO Box 2034 Lake Oswego, OR 97035

INDICATIONS

For the temporary relief of mild pain, inflammation, or stiffness in joints, muscles, or surrounding tissue, particularly when improved by applying cold.*

PURPOSE

*Claims based on traditional homeopathic practice, not accepted medical evidence. Not FDA evaluated.

WARNINGS

In case of overdose, get medical help or contact a poison control center right away.

Keep out of the reach of children.

PREGNANCY OR BREAST FEEDING

If pregnant or breastfeeding, ask a healthcare professional before use.

DIRECTIONS

Place drops under tongue 30 minutes before/after meals. Adults and children 12 years and over: Take 10 drops up to 3 times per day for up to 6 weeks. For immediate onset of symptoms, take 10 to 15 drops every 15 minutes up to 3 hours. For less severe symptoms, take 10-15 drops hourly up to 8 hours. Consult a physician for use in children under 12 years of age.

OTHER INFORMATION

Tamper resistant. If seal is broken, do not use. After opening, close container tightly and store at room temperature away from heat.

INACTIVE INGREDIENTS

20% ethanol, purified water.

LABEL

Est 1985

Professional Formulas

Complementary Health

Rheuma Pain II Drops

Homeopathic Remedy

2 FL. OZ. (59 mL)